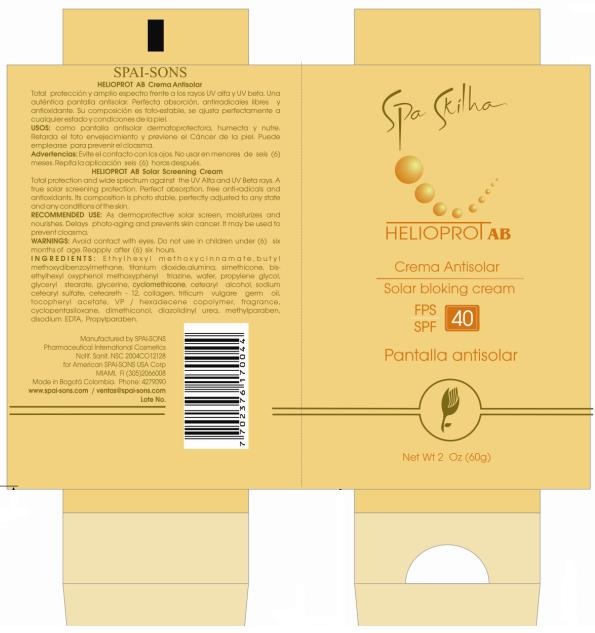 DRUG LABEL: SPA SKILHA 
NDC: 66854-025 | Form: CREAM
Manufacturer: SPAI-SONS PHARMACEUTICAL INTERNATIONAL COSMETICS
Category: otc | Type: HUMAN OTC DRUG LABEL
Date: 20120607

ACTIVE INGREDIENTS: BEMOTRIZINOL 1.5 g/100 g; OCTINOXATE 7.5 g/100 g; AVOBENZONE 4 g/100 g; TITANIUM DIOXIDE 2.0 g/100 g
INACTIVE INGREDIENTS: ALUMINUM OXIDE; DIMETHICONE; SILICON DIOXIDE; WATER; PROPYLENE GLYCOL; GLYCERYL MONOSTEARATE; GLYCERIN; CYCLOMETHICONE; CETOSTEARYL ALCOHOL; SODIUM CETOSTEARYL SULFATE; CETEARETH-12; HYDROLYSED BOVINE COLLAGEN (ENZYMATIC; 2000-5000 MW); WHEAT GERM OIL; .ALPHA.-TOCOPHEROL ACETATE, D-; CYCLOMETHICONE 5; DIMETHICONOL (41 MPA.S); DIAZOLIDINYL UREA; METHYLPARABEN; EDETATE DISODIUM; PROPYLPARABEN

SPA SKILHA HELIOPROT AB SPF 40

ACTIVE INGREDIENT

Ethylhexyl methoxycinnamate, butyl methoxydibenzoylmethane, titanium dioxide and bis-ethylhexyl oxyphenol methoxyphenyl triazine offers total protection and wide spectrum against the UVA and UVB.

PURPOSE

As dermoprotective solar screen, moisturizes and nourishes. Delays photo-aging and prevents skin cancer.

Keep out of reach of children

INDICATIONS AND USAGE

Use this product when you exposed to the sun. SPF 40 UVA / UVB

WARNINGS

Avoid contact with eyes, do not use in the children under (6) six months of age.

DOSAGE AND ADMINISTRATION

- Apply generously before sun exposure.
- Reapply after (6) six hours.

INACTIVE INGREDIENT

Its composition is photo stable, perfectly adjusted to any state and any contidtion of the skin.

IMAGE OF THE LABEL